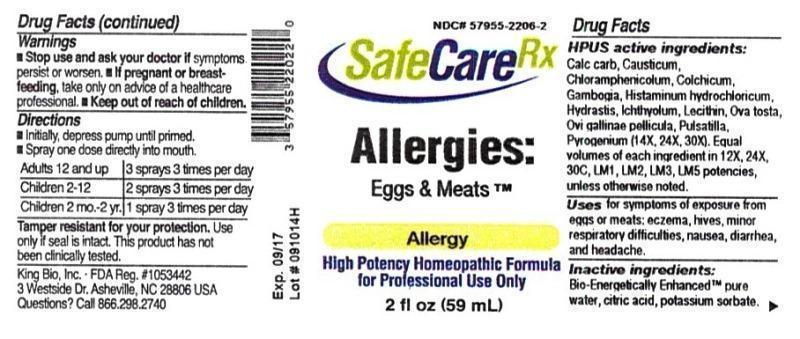 DRUG LABEL: Allergies Eggs and Meats
NDC: 57955-2206 | Form: LIQUID
Manufacturer: King Bio Inc.
Category: homeopathic | Type: HUMAN OTC DRUG LABEL
Date: 20150126

ACTIVE INGREDIENTS: OYSTER SHELL CALCIUM CARBONATE, CRUDE 12 [hp_X]/59 mL; CAUSTICUM 12 [hp_X]/59 mL; CHLORAMPHENICOL 12 [hp_X]/59 mL; COLCHICUM AUTUMNALE BULB 12 [hp_X]/59 mL; GAMBOGE 12 [hp_X]/59 mL; HISTAMINE DIHYDROCHLORIDE 12 [hp_X]/59 mL; GOLDENSEAL 12 [hp_X]/59 mL; ICHTHAMMOL 12 [hp_X]/59 mL; EGG PHOSPHOLIPIDS 12 [hp_X]/59 mL; EGG SHELL, COOKED 12 [hp_X]/59 mL; EGG SHELL MEMBRANE 12 [hp_X]/59 mL; PULSATILLA VULGARIS 12 [hp_X]/59 mL; RANCID BEEF 14 [hp_X]/59 mL
INACTIVE INGREDIENTS: WATER; ANHYDROUS CITRIC ACID; POTASSIUM SORBATE

Allergies Eggs and Meats™

ACTIVE INGREDIENT

Drug Facts__________________________________________________________________________________________________________

HPUS activeingredients: Calcarea carbonica, Causticum, Chloramphenicolum, Colchicum autumnale, Gambogia, Histaminum hydrochloricum, Hydrastis canadensis, Ichthyolum, Lecithin, Ova tosta, Ovi gallinae pellicula, Pulsatilla, Pyrogenium (14X, 24X, 30X). Equal volumes of each ingredient in 12X, 24X, 30C, LM1, LM2, LM3, LM5 potencies, unless otherwise noted.

INDICATIONS AND USAGE

Uses for symptoms of exposure from eggs or meats: eczema, hives, minor respiratory difficulties, nausea, diarrhea, and headache.

Inactive Ingredients:

Bio-Energetically Enhanced™ pure water, citric acid and potassium sorbate.

Warnings

- Stop use and ask your doctor if symptoms persist or worsen.
- If pregnant or breast-feeding, take only on advice of a healthcare professional.

- Keep out of reach of children.

Directions

- Initially, depress pump until primed.
- Spray one dose directly into mouth.
- Adults 12 and up- 3 sprays 3 times per day
- Children 2-12 -2 sprays 3 times per day
- Children 2 mo.- 2 yr.-1 spray 3 times per day

OTHER SAFETY INFORMATION

Tamper resistant for your protection. Use only if safety seal is intact. This product has not been clinically tested.

PURPOSE

Uses for symptoms of exposure from eggs or meats:

- eczema
- hives
- minor respiratory difficulties
- nausea
- diarrhea
- headache